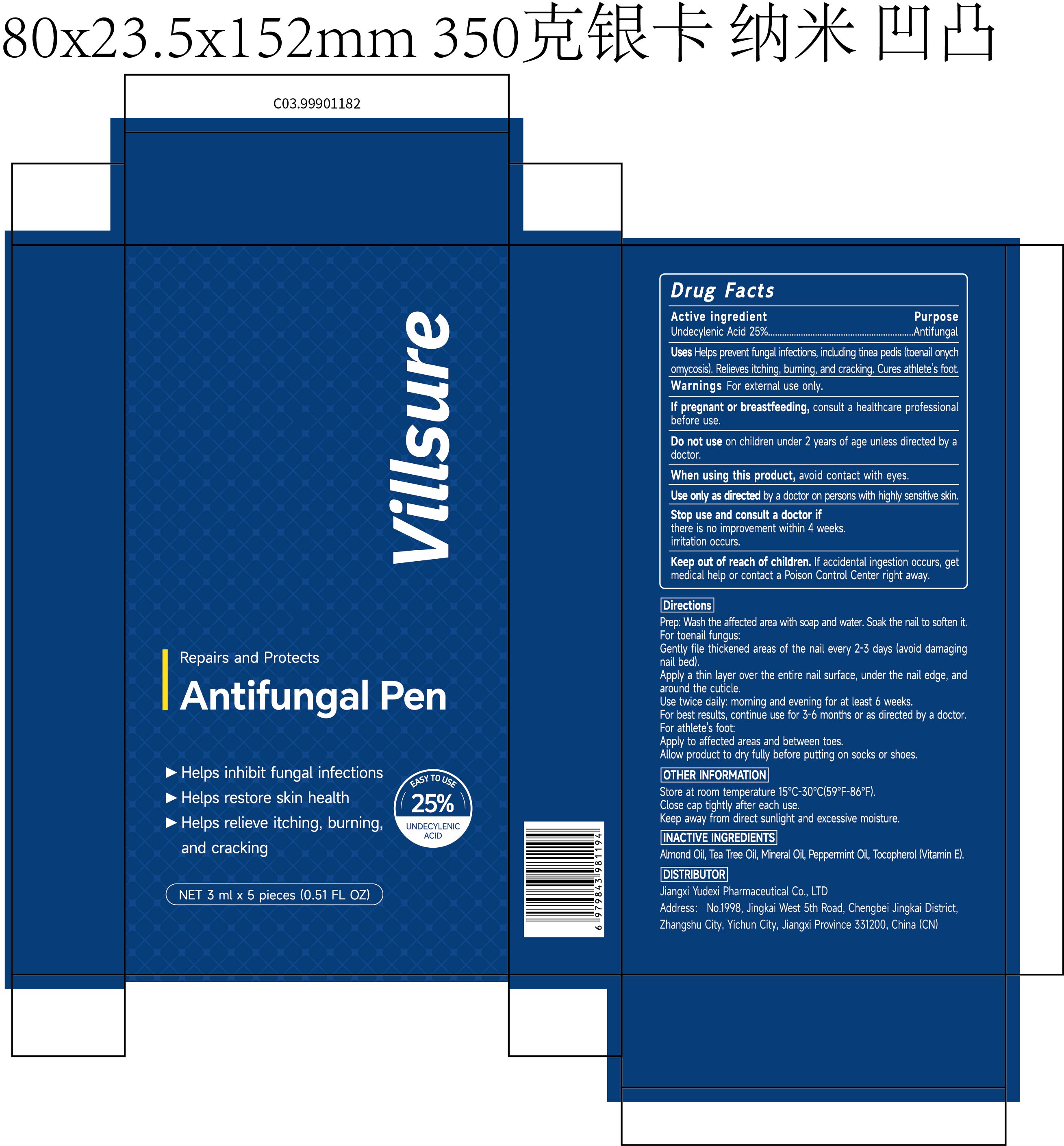 DRUG LABEL: ViLLsure Antifungal Pen
NDC: 85248-144 | Form: LIQUID
Manufacturer: Jiangxi Yudexi Pharmaceutical Co., LTD
Category: otc | Type: HUMAN OTC DRUG LABEL
Date: 20260224

ACTIVE INGREDIENTS: UNDECYLENIC ACID 25 g/100 mL
INACTIVE INGREDIENTS: PEPPERMINT OIL; TEA TREE OIL; MINERAL OIL; ALMOND OIL; TOCOPHEROL

85248-144

Active Ingredient

Undecylenic acid 25%

Purpose

Antifungal

Use

Helps prevent fungal infections, incuding tinea pedis (toenail onych omycosis). Relieves itching, burning, and cracking. Cures athlete's foot

Warnings

For external use only. If pregnant or breastfeeding, consult a healthcare professional before use.

Do not use

on children under 2 years of age unless directed by a doctor.

When Using

avoid contact with eyes.

Stop Use

there is no improvement within 4 weeks.iritation occurs.

Ask Doctor

there is no improvement within 4 weeks.iritation occurs.

Keep Oot Of Reach Of Children

lf accidental ingestion occurs, get medical help or contact a Poison Control Center right away.

Directions

Prep: Wash the affected area with soap and water. Soak the nail to soften it.For toenail fungus:Gently file thickened areas of the nail every 2-3 days (avoid damaging nail bed). Apply a thin laver over the entire nail surface, under the nail edge, and around the cuticle. Use twice daily:morning and evening for at least 6 weeks. For best results,continue use for 3-6 months or as directed by a doctor.For athlete's foot: Apply to affected areas and between toes. Allow product to dry fully before putting on socks or shoes.

Other information

Store at room temperature 15℃-30℃(59ºF-86ºF). Close cap tightly after each use.Keep away from direct sunlight and excessive moisture.

Inactive ingredients

Almond Oil, Tea Tree Oil, Mineral Oil, Peppermint Oil, Tocopherol (Vitamin E).